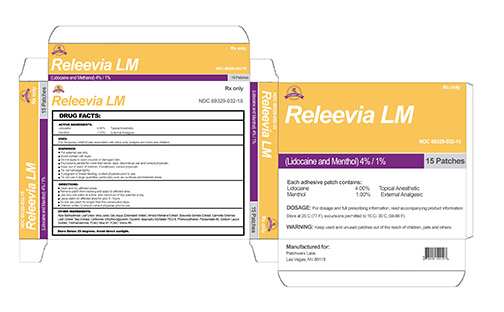 DRUG LABEL: Releevia LM Patch
NDC: 69329-032 | Form: PATCH
Manufacturer: Patchwerx Labs, Inc.
Category: prescription | Type: HUMAN PRESCRIPTION DRUG LABEL
Date: 20150308

ACTIVE INGREDIENTS: LIDOCAINE HYDROCHLORIDE 4 g/100 g; MENTHOL 1 g/100 g
INACTIVE INGREDIENTS: WATER; GLYCERIN; ARNICA MONTANA; POLYSORBATE 80; ALOE VERA LEAF; BOSWELLIA SACRA WHOLE; GREEN TEA LEAF; CARBOMER 1342; ETHYLHEXYLGLYCERIN; ISOPROPYL MYRISTATE; PEG-8 GLYCERYL ISOSTEARATE; PHENOXYETHANOL; SODIUM LAURYL SULFATE; TRIETHANOLAMINE BENZOATE; FD&C BLUE NO. 1; FD&C YELLOW NO. 5

Releevia LM Patch

Warnings

For external use only

Avoid contact with eyes

Do not applly to open wounds or damaged skin

If symptoms persist for more than seven days, discontinue use and consult physician

If swallowed, consult physician

Do not bandage tightly

If pregnant or breast feeding, contact physician prior to use

Do not use in large quantities, particularly over raw surfaces or blistered areas

Keep out of reach of children

ACTIVE INGREDIENT

Lidocaine HCL 4.00%

Menthol 1.00%

INACTIVE INGREDIENT

aloe barbadensis leaf, water, arnica montan extract, boswella serrata extract, camelia sinensis leaf extract, carbomer, ethylhexylglycerine, glycerine, isopropyl myristate, PEG 8, phenoxyethanol, polysorbate 80, sodium lauryl sulfate, triethanolamine, fd&c blue #1, fd&c yellow #5

DOSAGE AND ADMINISTRATION

clean and dry affected area

remove patch from backing and apply to affected area

use only one patch at a time, and maximum of four patches/day

leave patch on affected area for up to 8 hours

do not use patches for longer than five consecutive days

children under 12 should consult physician prior to use

INDICATIONS AND USAGE

Temporary relief of pain associated with minor cuts, scrapes and minor skin irritations

PURPOSE

Topical anesthetic

External analgesic